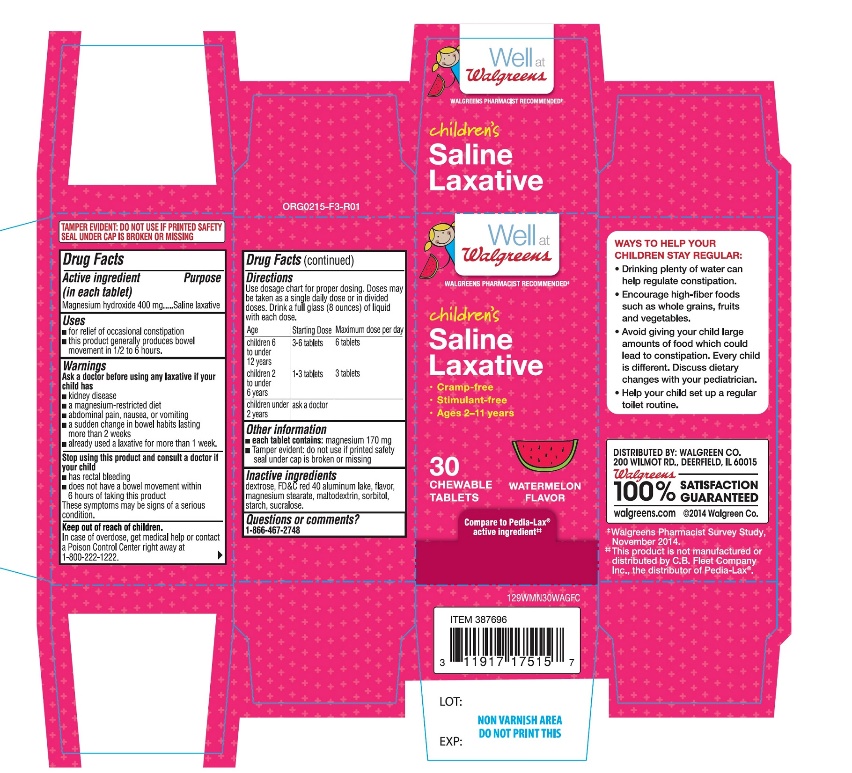 DRUG LABEL: Walgreens Childrens

NDC: 0363-9129 | Form: TABLET, CHEWABLE
Manufacturer: WALGREEN CO.
Category: otc | Type: HUMAN OTC DRUG LABEL
Date: 20251125

ACTIVE INGREDIENTS: MAGNESIUM HYDROXIDE 400 mg/1 1
INACTIVE INGREDIENTS: DEXTROSE, UNSPECIFIED FORM; FD&C RED NO. 40; WATERMELON; MAGNESIUM STEARATE; MALTODEXTRIN; SORBITOL; STARCH, CORN; SUCRALOSE

Children’s Saline Laxative Chewable Tablets

Active Ingredient

Magnesium hydroxide 400 mg

Purpose

Saline laxative

Uses

- for relief of occasional constipation
- this product usually produces bowel movement in 1/2 to 6 hours

Warnings

Ask a doctor before using any laxative if child has

- kidney disease
- a magnesium-restricted diet
- abdominal pain, nausea or vomiting
- a sudden change in bowel habits lasting more than 2 weeks
- constipation continues after 1 week of use, contact your child's doctor
- already used a laxative for more than 1 week

Stop use and consult a doctor if your child has

- rectal bleeding
- no bowel movement within 6 hours of taking this product

These symptoms may indicate a serious condition.

Keep out of reach of children

In case of overdose, get medical help or contact a Poison Control Center right away at 1-800-222-1222.

Directions

Use dosage chart for proper dosing. Doses may be taken as a single daily dose or in divided doses. Drink a full glass (8 ounces) of liquid with each dose.

Age | Starting dose | Maximum dose per day
children 6 to under 12 years | 3-6 tablets | 6 tablets
children 2 to under 6 years | 1-3 tablets | 3 tablets
children under 2 years | ask a doctor

Other information

- each tablet contains: 170 mg of magnesium
- Tamper evident: do not use if printed safety seal under cap is broken or missing.

Inactive ingredients

dextrose, FD&C red 40 aluminum lake, flavor, magnesium stearate, maltodextrin, sorbitol, starch, sucralose.

Questions or comments?

1-866-467-2748

PRINCIPAL DISPLAY PANEL

Well at

Walgreens

WALGREEN PHARMACIST RECOMMENDED

NDC# 0363-9129-30

Children’s

Saline Laxative

- Cramp-free
- Stimulant-free
- Ages 2-11 years

30 CHEWABLE TABLETS

WATERMELON FLAVOR

Compare to Pedia-Lax®active ingredient‡

DISTRIBUTED BY: WALGREEN CO.

200 WILMOT RD., DEERFIELD, IL 60015

Walgreens

100% SATISFACTION GUARANTEED

Walgreens.com ©2014 Walgreen Co.

‡Walgreens Pharmacist Survey Study, November 2014.

‡This product is not manufactured or distributed by C.B. Fleet Company Inc., the distributor of Pedia-Lax®.